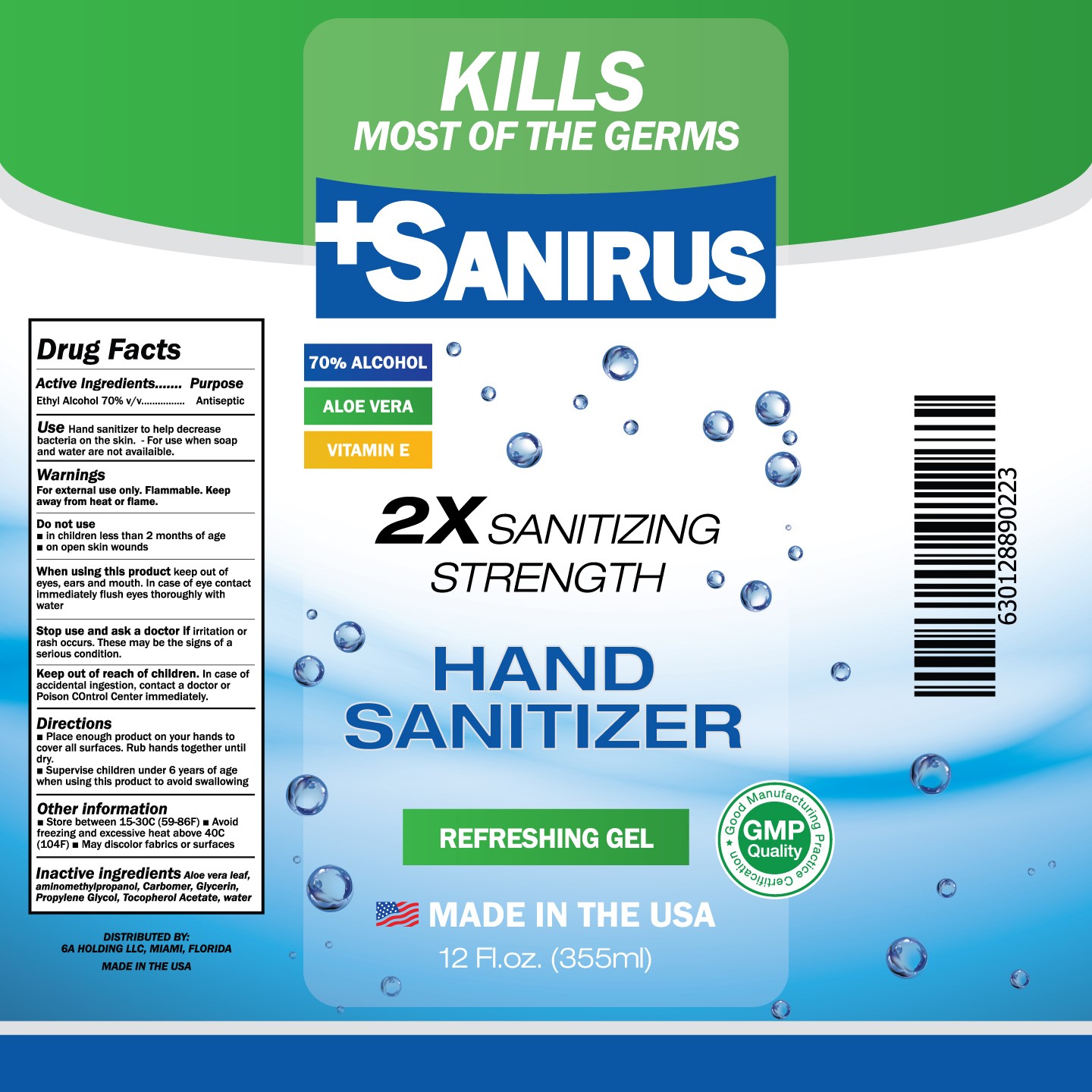 DRUG LABEL: Sanirus Hand Sanitizer
NDC: 74691-001 | Form: GEL
Manufacturer: 6A Holding, LLC
Category: otc | Type: HUMAN OTC DRUG LABEL
Date: 20200417

ACTIVE INGREDIENTS: ALCOHOL 70 mL/100 mL
INACTIVE INGREDIENTS: GLYCERIN; ALOE VERA LEAF; WATER; CARBOMER HOMOPOLYMER, UNSPECIFIED TYPE; AMINOMETHYLPROPANOL; PROPYLENE GLYCOL; .ALPHA.-TOCOPHEROL ACETATE

Sanirus Hand Sanitizer

Active Ingredient

Ethyl Alcohol 70% v/v

Purpose

Antiseptic

Use

Hand Sanitizer to help decrease bacteria on the skin. For use when soap and water are not available.

Warnings

For external use only. Flammable. Keep away from heat or flame.

Do not use

■ In children less than 2 months of age

■ on open skin wounds

When using this product

keep out of eyes ears and mouth. In case of eye contact immediately flush eyes throughly with water

Stop use and ask a doctor if

irritation or rash occurs. These may be signs of a serious condition

Keep out of reach of children

In case of accidental ingestion, contact a doctor or Poison Control Center immediately.

Directions

■ Place enough product on your hands to cover all surfaces. Rub hands together until dry ■ Supervise children under 6 years of age when using this product to aviod swallowing.

Other information

■ Store between 15-30C (59-89F) ■ Avoid freezing and excessive heat above 40C (104F) ■ May discolor fabrics or surfaces

Inactive ingredients

Aloe vera leaf, Aminomethylpropanol, Carbomer, Gycerin, Propylene Glycol, Tocopherol Acetate, Water